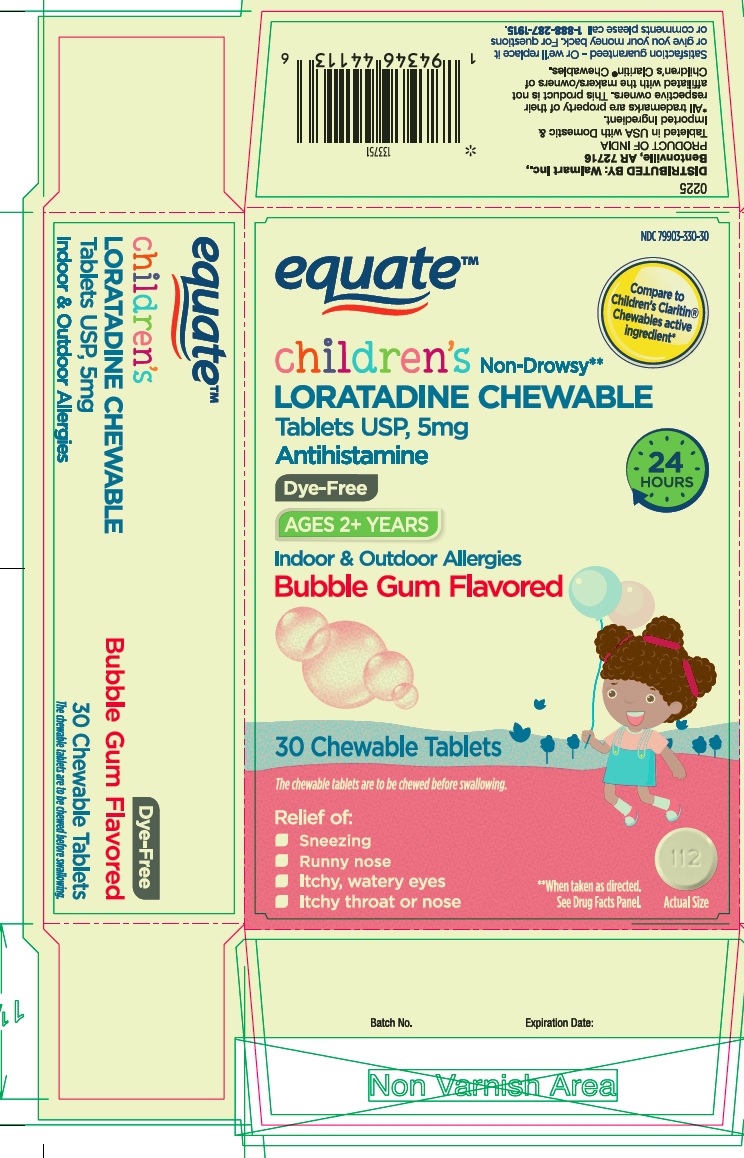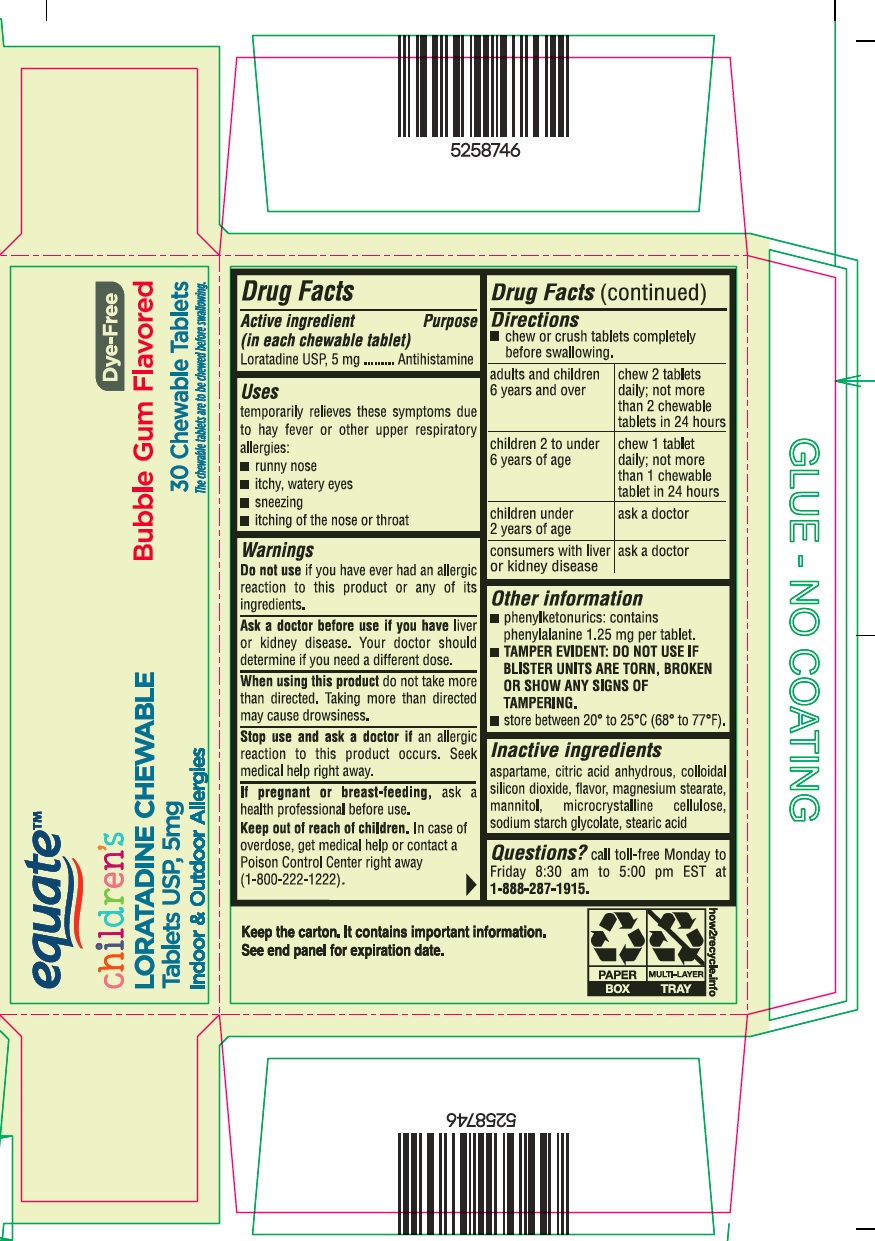 DRUG LABEL: DYE-FREE CHILDRENS LORATADINE
NDC: 79903-330 | Form: TABLET, CHEWABLE
Manufacturer: WAL-MART STORES, INC
Category: otc | Type: HUMAN OTC DRUG LABEL
Date: 20250404

ACTIVE INGREDIENTS: LORATADINE 5 mg/1 1
INACTIVE INGREDIENTS: ASPARTAME; ANHYDROUS CITRIC ACID; SILICON DIOXIDE; MAGNESIUM STEARATE; MANNITOL; MICROCRYSTALLINE CELLULOSE; SODIUM STARCH GLYCOLATE TYPE A POTATO; STEARIC ACID

DYE-FREE CHILDRENS LORATADINE

Drug Facts

Active Ingredient (in each chewable tablet)

Loratadine USP, 5 mg

Purpose

Antihistamine

Uses

temporarily relieves these symptoms due to hay fever or other upper respiratory allergies:

- runny nose
- itchy, watery eyes
- sneezing
- itching of the nose or throat

Warnings

DO NOT USE

Do not useif you have ever had an allergic reaction to this product or any of its ingredients.

Ask a doctor before use if you haveliver or kidney disease. Your doctor should determine if you need a different dose.

WHEN USING

When using this productdo not take more than directed. Taking more than directed may cause drowsiness.

Stop use and ask a doctor ifan allergic reaction to this product occurs. Seek medical help right away.

PREGNANCY OR BREAST FEEDING

If pregnant or breast-feeding,ask a health professional before use.

Keep out of reach of children.In case of overdose, get medical help or contact a Poison Control Center right away (1-800-222-1222).

Directions

- chew or crush tablets completely before swallowing.

adults and children 6 years and over | chew 2 tablets daily; not more than 2 chewable tablets in 24 hours
children 2 to under 6 years of age | chew 1 tablet daily; not more than 1 chewable tablet in 24 hours
children under 2 years of age | ask a doctor
consumers with liver or kidney disease | ask a doctor

Other Information

- phenylketonurics: contains phenylalanine 1.25 mg per tablet.
- TAMPER EVIDENT: DO NOT USE IF BLISTER UNITS ARE TORN, BROKEN OR SHOW ANY SIGNS OF TAMPERING.
- store between 20° to 25°C (68° to 77°F).

Inactive Ingredients

aspartame, citric acid anhydrous, colloidal silicon dioxide, flavor, magnesium stearate, mannitol, microcrystalline cellulose, sodium starch glycolate, stearic acid

Questions?

Call toll-free Monday to Friday 8:30 am to 5:00 pm EST at 1-888-287-1915.

DISTRIBUTED BY: Walmart Inc., Bentonville, AR 72716

PRINCIPAL DISPLAY PANEL - 5 mg Tablet Blister Pack Carton

NDC 79903-330-30

equate™

Compare to
Children's Claritin®
Chewables active
ingredient*

childrens Non-Drowsy**
LORATADINE CHEWABLE
Tablets USP, 5mg
Antihistamine

24
HOURS

Dye-Free

AGES 2+ YEARS

Indoor & Outdoor Allergies

Bubble Gum Flavored

30 Chewable Tablets

The chewable tablets are to be chewed before swallowing.

Relief of:

- Sneezing
- Runny nose
- Itchy, watery eyes
- Itchy throat or nose

**When taken as directed.
See Drug Facts Panel.